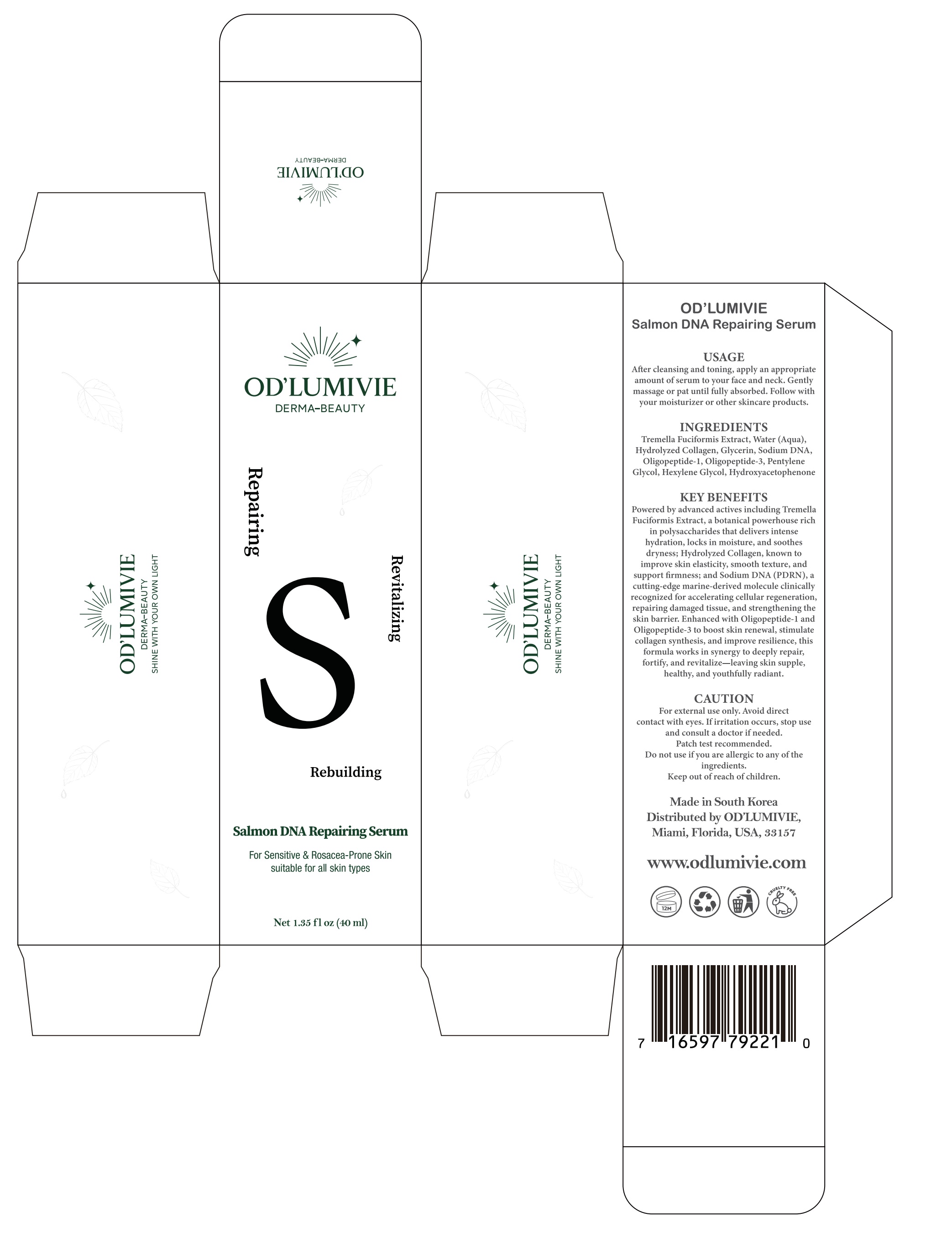 DRUG LABEL: ODLUMIVIE Salmon DNA Repairing Serum
NDC: 87036-028 | Form: LIQUID
Manufacturer: OD’LUMIVIE
Category: otc | Type: HUMAN OTC DRUG LABEL
Date: 20251111

ACTIVE INGREDIENTS: RH-OLIGOPEPTIDE-1 1 g/100 mL
INACTIVE INGREDIENTS: HYDROXYACETOPHENONE; HEXYLENE GLYCOL; MARINE COLLAGEN, SOLUBLE; PENTYLENE GLYCOL; WATER; TREMELLA FUCIFORMIS WHOLE; GLYCERIN

ACTIVE INGREDIENT

INACTIVE INGREDIENT

INGREDIENTS
Tremella Fuciformis Extract, Water (Aqua),Hydrolyzed Collagen, Glycerin, Sodium DNA,Oligopeptide-1, Oligopeptide-3, PentyleneGlycol, Hexylene Glycol, Hydroxyacetophenone

PURPOSE

KEY BENEFITSPowered by advanced actives including TremellaFuciformis Extract, a botanical powerhouse richin polysaccharides that delivers intensehydration, locks in moisture, and soothesdryness; Hydrolyzed Collagen, known toimprove skin elasticity, smooth texture, andsupport frmness; and Sodium DNA (PDRN),acutting-edge marine-derived molecule clinicallyrecognized for accelerating cellular regeneration,repairing damaged tissue, and strengthening theskin barrier, Enhanced with Oligopeptide-l andOligopeptide-3 to boost skin renewal, stimulatecollagen synthesis, and improve resilience, thisformula works in synergy to deeply repair,fortify, and revitalize-leaving skin supple,healthy, and youthfully radiant.

WARNINGS

CAUTION
For external use only, Avoid direct contact with eyes. Ifirritation occurs, stop useand consult a doctor if needed. Patch test recommended, Do not use if you areallergic to any of the ingredients. Keep out of reach of children.

DO NOT USE

CAUTION
For external use only, Avoid direct contact with eyes. Ifirritation occurs, stop useand consult a doctor if needed. Patch test recommended, Do not use if you areallergic to any of the ingredients. Keep out of reach of children.

KEEP OUT OF REACH OF CHILDREN

CAUTION
For external use only, Avoid direct contact with eyes. Ifirritation occurs, stop useand consult a doctor if needed. Patch test recommended, Do not use if you areallergic to any of the ingredients. Keep out of reach of children.

STOP USE

CAUTION
For external use only, Avoid direct contact with eyes. Ifirritation occurs, stop useand consult a doctor if needed. Patch test recommended, Do not use if you areallergic to any of the ingredients. Keep out of reach of children.

USAGE
After cleansing and toning, apply an appropriateamount of serum to your face and neck. Gentlymassage or pat until fully absorbed. Follow withyour moisturizer or other skincare products.

WHEN USING

USAGE
After cleansing and toning, apply an appropriateamount of serum to your face and neck. Gentlymassage or pat until fully absorbed. Follow withyour moisturizer or other skincare products.

DOSAGE AND ADMINISTRATION

USAGE
After cleansing and toning, apply an appropriateamount of serum to your face and neck. Gentlymassage or pat until fully absorbed. Follow withyour moisturizer or other skincare products.

PACKAGE LABEL

USAGE
OD'LUMIVIE
DERMA-BEAUTY
Repairing
、
Revitalizing
Rebuilding
Salmon DNA Repairing Serum
For Sensitive & Rosacea-Prone Skinsuitable for all skin types
IIAIWATGO
LH9I NMO HNOA HLIM 3NIHSALny38-VW830
After cleansing and toning, apply an appropriateamount ofserum to your face and neck, Gentlymassage or pat until fully absorbed. Follow withyour moisturizer or other skincare products.
INGREDIENTS
Tremella Fuciformis Extract,Water(Aqua)Hydrolyzed Collagen, Glycerin, Sodium DNAOligopeptide-1, Oligopeptide-3, PentyleneGlycol,Hexylene Glycol,Hydroxyacetophenone
KEY BENEFITS
Powered by advanced actives including TremellaFuciformis Extract, a botanical powerhouse richin polysaccharides that delivers intensehydration,locks in moisture, and soothes
dryness:Hydrolyzed Collagen, known toimprove skin elasticity,smooth texture, andsupport firmness; and Sodium DNA(PDRN).acutting-edge marine-derived molecule clinicallyrecognized for accelerating cellular regenerationrepairing damaged tissue,and strengthening theskin barrier.Enhanced with Oligopeptide-l andOligopeptide-3 to boost skin renewal, stimulatecollagen synthesis,and improve resilience, thisformula works in synergy to deeply repair,fortify, and revitalize-leaving skin supple.healthy,and youthfully radiant.
CAUTION
For external use only, Avoid direetcontact with eyes. Ifirritation occurs, stop useand consult a doctor ifneeded.Patch test recommended.Do not use if you are allergic to any ofthe
ingredients.
Keep out ofreach ofchildren.
Made in South KoreaDistributed by ODTUMIIEMiami.Florida.USA.33157
wwwodlumivie.com